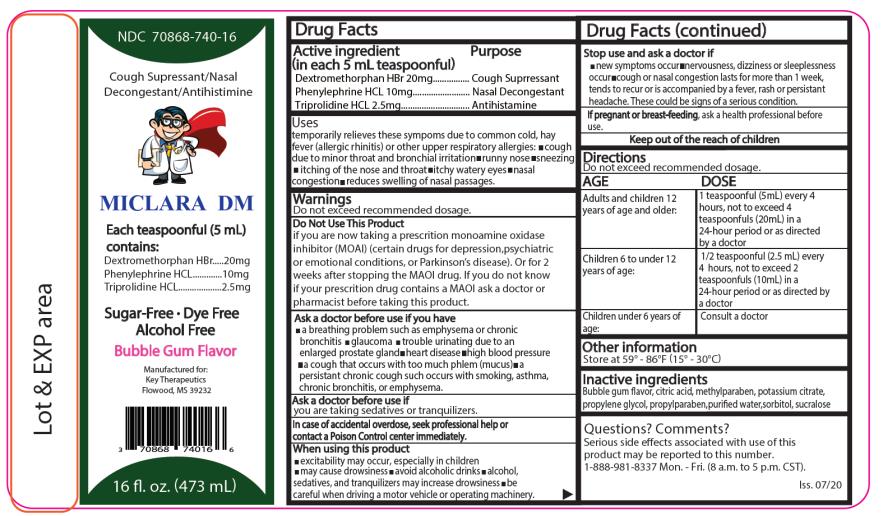 DRUG LABEL: Miclara DM
NDC: 70868-740 | Form: LIQUID
Manufacturer: Key Therapeutics
Category: otc | Type: HUMAN OTC DRUG LABEL
Date: 20220126

ACTIVE INGREDIENTS: DEXTROMETHORPHAN HYDROBROMIDE 20 mg/5 mL; PHENYLEPHRINE HYDROCHLORIDE 10 mg/5 mL; TRIPROLIDINE HYDROCHLORIDE 2.5 mg/5 mL
INACTIVE INGREDIENTS: CITRIC ACID MONOHYDRATE; METHYLPARABEN; POTASSIUM CITRATE; PROPYLENE GLYCOL; PROPYLPARABEN; WATER; SORBITOL; SUCRALOSE

Miclara DM

MICLARA LQ LIQUID

Drug Facts

Active ingredients

(in each 5 mL teaspoonful)

Dextromethorphan HBr 20mg

Phenylephrine HCl 10mg

Triprolidine HCl 2.5 mg

Uses

temporarily relieves these symptoms due to common cold, hay fever (allergic rhinitis) or other upper respiratory allergies:

- cough due to minor throat or bronchial irritation
- runny nose
- sneezing
- itching of the nose or throat
- itchy, watery eyes
- nasal congestion
- reduces swelling of nasal passages

Warnings

Do not exceed recommended dosage.

Do not use this product

If you are now taking a prescription monoamine oxidase inhibitor (MAOI) (certain drugs for depression, psychiatric, or emotional conditions, or Parkinson's disease), or for 2 weeks after stopping the MAOI drug. If you do not know if your prescription drug contains an MAOI, ask a doctor or pharmacist before giving this product.

Ask a doctor before use if you have

- a breathing problem such as emphysema or chronic bronchitis
- glaucoma
- trouble urinating due to an enlarged prostate gland
- heart disease
- high blood pressure
- a cough that occurs with too much phlegm (mucus)
- a persistent chronic cough such occurs with smoking, asthma, chronic bronchitis, or emphysema

Ask a doctor before use

if you are taking sedatives or tranquilizers.

When using this product

- excitability may occur, especially in children
- may cause drowsiness
- avoid alcoholic drinks
- alcohol, sedatives, and tranquilizers may increase drowsiness
- be careful when driving a motor vehicle or operating machinery

Stop use and ask a doctor if

- new symptoms occur
- nervousness, dizziness, or sleeplessness occur
- Cough or nasal congestion lasts for more than 1 week, tends to recur or is accompanied by a fever, rash, or persistent headache. These could be signs of a serious condition.

If pregnant or breast-feeding, ask a health professional before use.

Keep out of the reach of children.

In case of accidental overdose seek professional help or contact a Poison Control Center immediately.

Directions

Do not exceed recommended dosage.

Age | Dose
Adults and children 12 years of age and older: | 1 teaspoonful (5mL) every 4 hours, not to exceed 4 teaspoonfuls (20mL) in a 24-hour period or as directed by a doctor
Children 6 to under 12 years of age: | ½ teaspoonful (2.5mL) every 4 hours, not to exceed 2 teaspoonfuls (10mL) in a 24-hour period or as directed by a doctor
Children under 6 years of age: | Consult a doctor

Other information

Store at 59° - 86°F (15° - 30°C)

Inactive ingredients

Bubble gum flavor, citric acid, methylparaben, potassium citrate, propylene glycol, propylparaben, purified water, sorbitol, sucralose.

Questions? Comments?

Serious side effects associated with use of this product may be reported to this number. Call 1-888-981-8337 Mon - Fri (8 a.m. to 5 p.m. CST)

PRINCIPAL DISPLAY PANEL

NDC 70868-740-16
MICLARA DM
Bubble gum flavor
16 fl oz (473 mL)